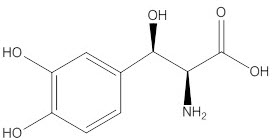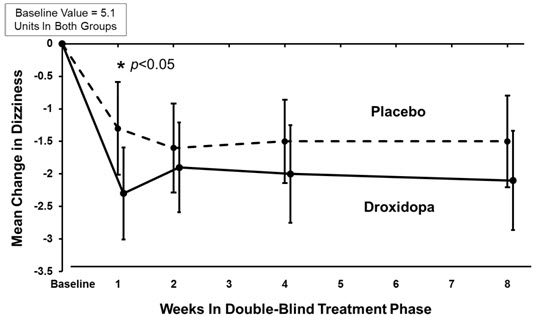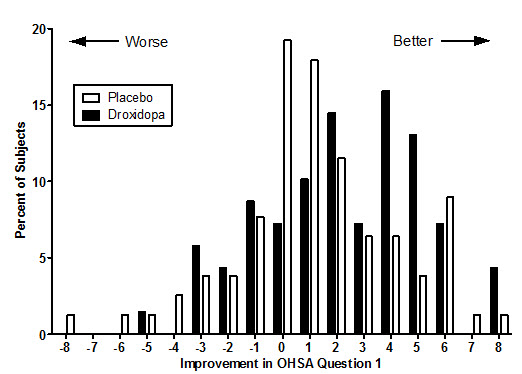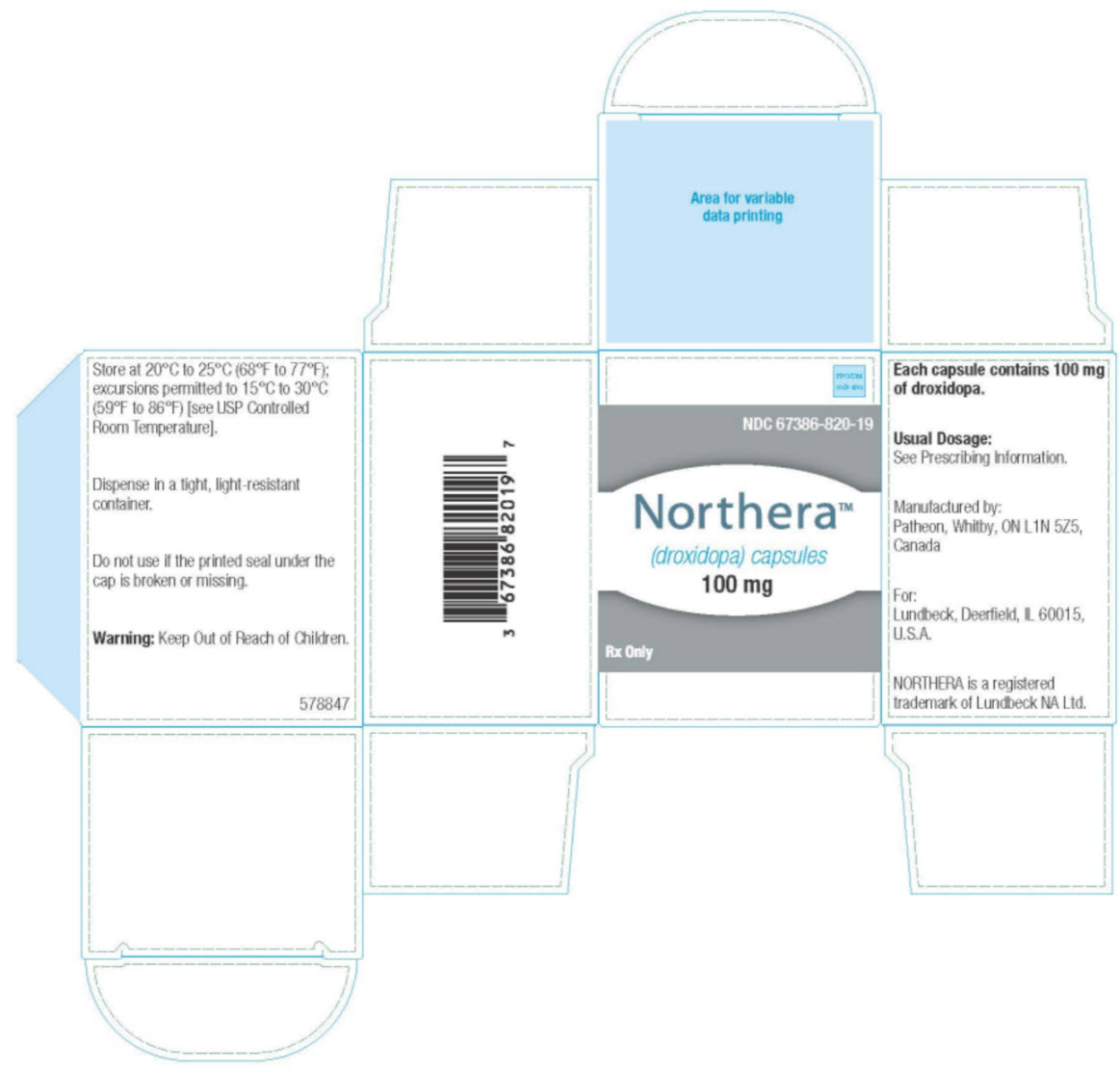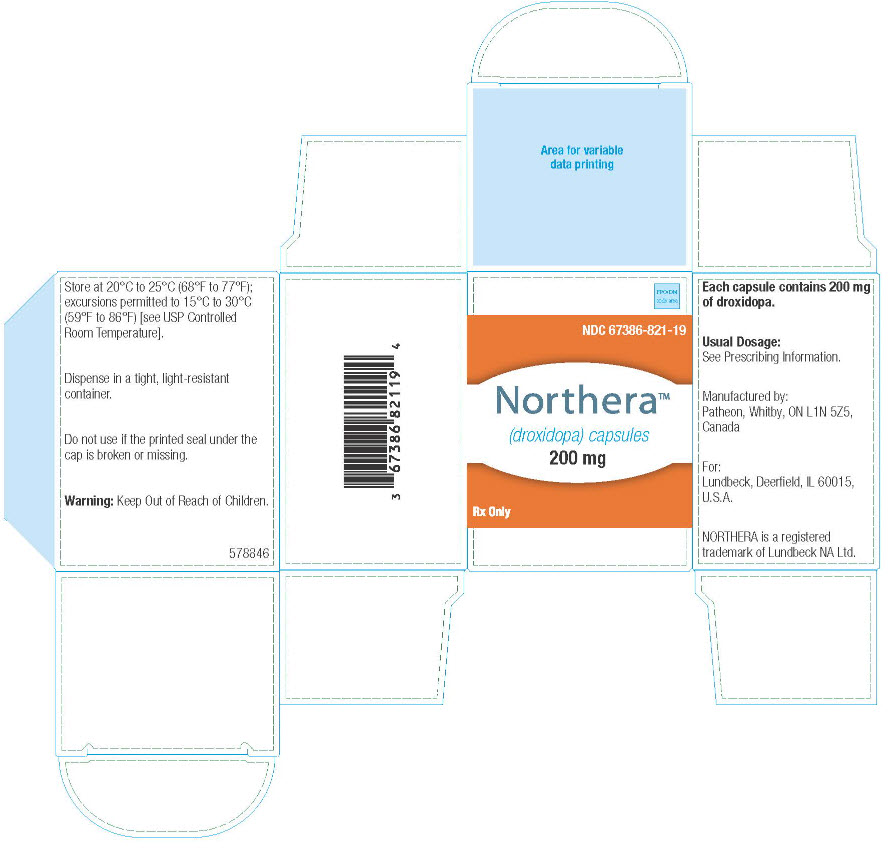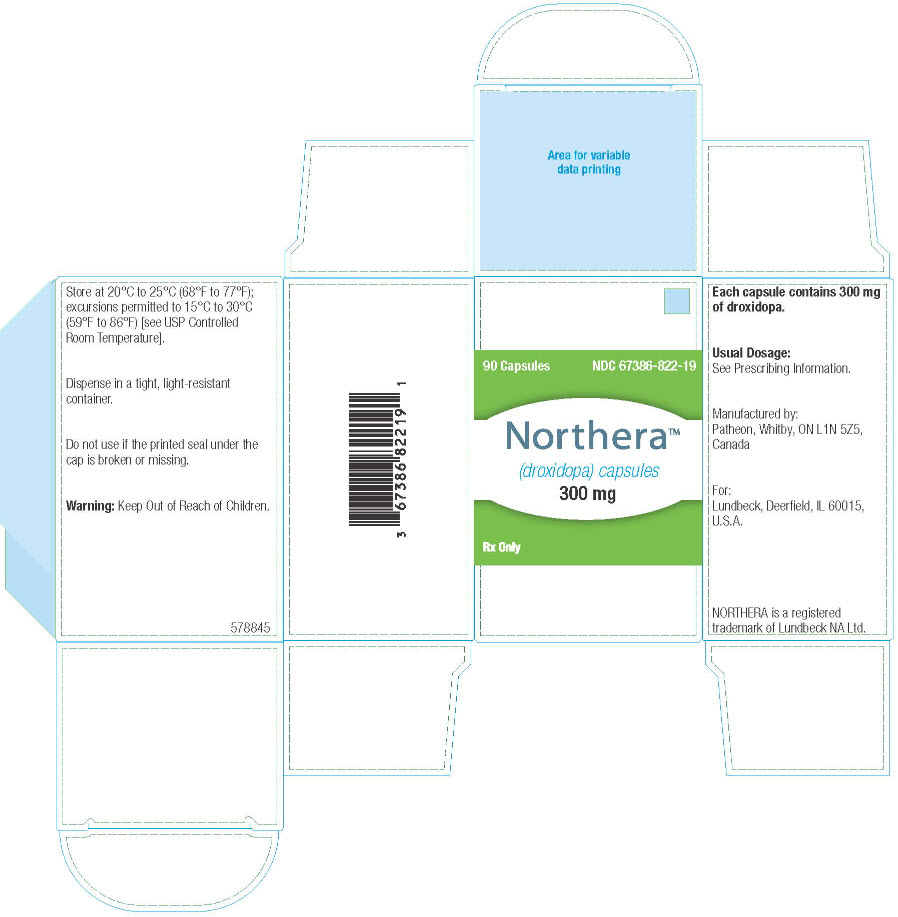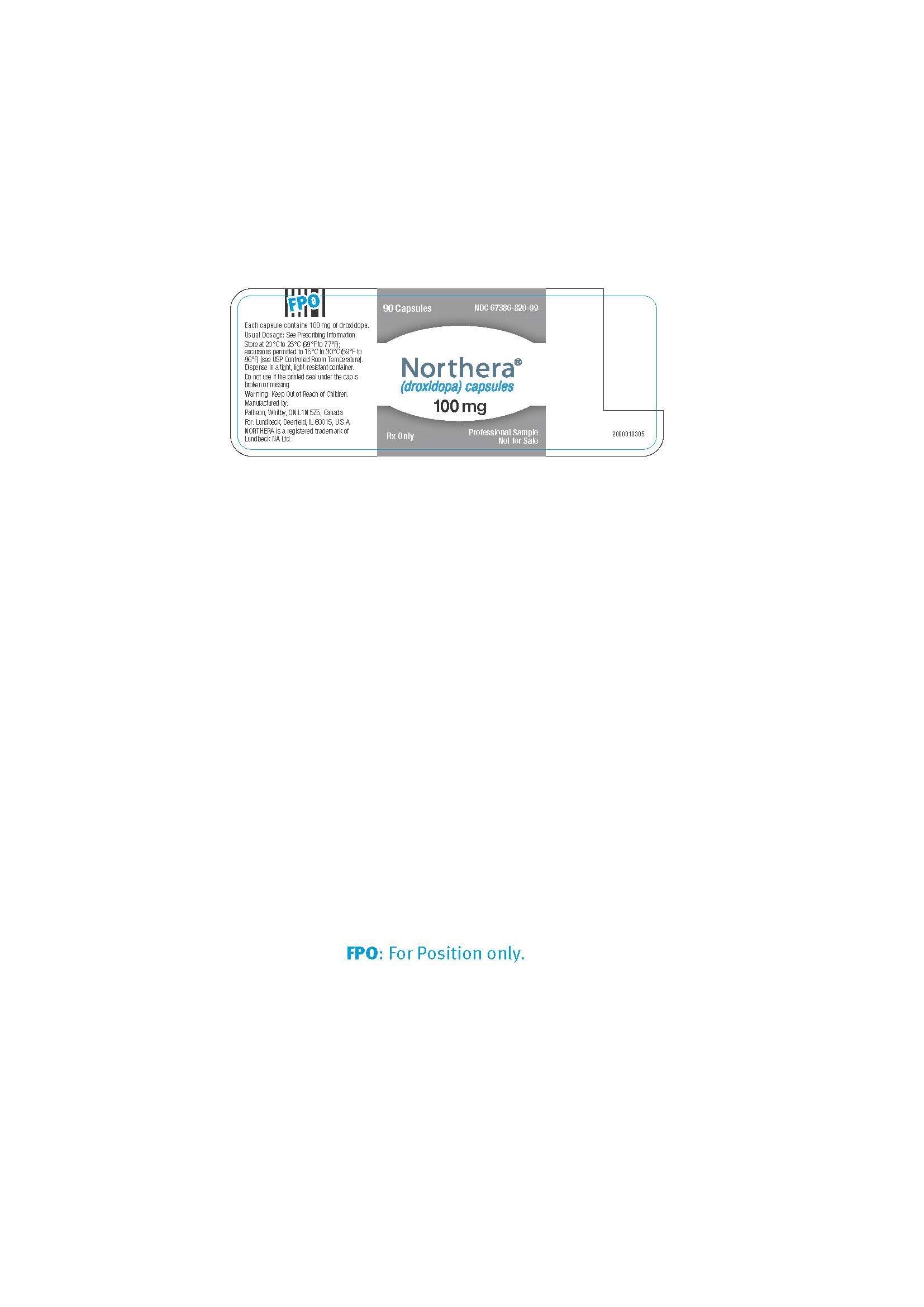 DRUG LABEL: Northera
NDC: 67386-820 | Form: CAPSULE
Manufacturer: Lundbeck Pharmaceuticals LLC
Category: prescription | Type: HUMAN PRESCRIPTION DRUG LABEL
Date: 20190701

ACTIVE INGREDIENTS: DROXIDOPA 100 mg/1 1
INACTIVE INGREDIENTS: MANNITOL; STARCH, CORN; MAGNESIUM STEARATE; GELATIN; TITANIUM DIOXIDE; FD&C BLUE NO. 2; FERRIC OXIDE RED; FERROSOFERRIC OXIDE

HIGHLIGHTS OF PRESCRIBING INFORMATION

These highlights do not include all the information needed to use NORTHERA® safely and effectively. See full prescribing information for NORTHERA.
NORTHERA® (droxidopa) capsules, for oral use
Initial U.S. Approval: 2014

WARNING: SUPINE HYPERTENSION

See full prescribing information for complete boxed warning.

Monitor supine blood pressure prior to and during treatment and more frequently when increasing doses. Elevating the head of the bed lessens the risk of supine hypertension, and blood pressure should be measured in this position. If supine hypertension cannot be managed by elevation of the head of the bed, reduce or discontinue NORTHERA [see Warnings and Precautions (5.1)].

1 INDICATIONS AND USAGE

NORTHERA is indicated for the treatment of orthostatic dizziness, lightheadedness, or the “feeling that you are about to black out” in adult patients with symptomatic neurogenic orthostatic hypotension (nOH) caused by primary autonomic failure (Parkinson's disease [PD], multiple system atrophy, and pure autonomic failure), dopamine beta-hydroxylase deficiency, and non-diabetic autonomic neuropathy. Effectiveness beyond 2 weeks of treatment has not been established. The continued effectiveness of NORTHERA should be assessed periodically (1).

2 DOSAGE AND ADMINISTRATION

- Starting dose is 100 mg three times during the day (2.1)
- Titrate by 100 mg three times daily, up to a maximum dose of 600 mg three times daily (2.1)
- Take consistently with or without food (2.1)
- To reduce the potential for supine hypertension, elevate the head of the bed and give the last dose at least 3 hours prior to bedtime (2.1)
- Take NORTHERA capsule whole (2.1)

3 DOSAGE FORMS AND STRENGTHS

- 100 mg, 200 mg, and 300 mg capsules (3)

4 CONTRAINDICATIONS

History of hypersensitivity to the drug or its ingredients (4)

5 WARNINGS AND PRECAUTIONS

- NORTHERA may cause supine hypertension and may increase cardiovascular risk if supine hypertension is not well-managed (5.1).
- Hyperpyrexia and confusion (5.2)
- May exacerbate symptoms in patients with existing ischemic heart disease, arrhythmias, and congestive heart failure (5.3)
- Allergic reactions (5.4)

6 ADVERSE REACTIONS

The most common adverse reactions (>5% and ≥3% compared to placebo) are headache, dizziness, nausea, and hypertension (6.1)

To report SUSPECTED ADVERSE REACTIONS, contact Lundbeck at 1-800-455-1141 or FDA at 1-800-FDA-1088 or www.fda.gov/medwatch.

7 DRUG INTERACTIONS

- Use of DOPA decarboxylase inhibitors may require dose adjustments for NORTHERA (7.2)

8 USE IN SPECIFIC POPULATIONS

- Lactation: Breastfeeding not recommended (8.2)
- Patients with Renal Impairment: Dosing recommendations cannot be provided for patients with GFR less than 30 mL/min (8.6)

FULL PRESCRIBING INFORMATION

WARNING: SUPINE HYPERTENSION

Monitor supine blood pressure prior to and during treatment and more frequently when increasing doses. Elevating the head of the bed lessens the risk of supine hypertension, and blood pressure should be measured in this position. If supine hypertension cannot be managed by elevation of the head of the bed, reduce or discontinue NORTHERA [see Warnings and Precautions (5.1)].

1 INDICATIONS AND USAGE

NORTHERA is indicated for the treatment of orthostatic dizziness, lightheadedness, or the “feeling that you are about to black out” in adult patients with symptomatic neurogenic orthostatic hypotension (nOH) caused by primary autonomic failure (Parkinson's disease [PD], multiple system atrophy, and pure autonomic failure), dopamine beta-hydroxylase deficiency, and non-diabetic autonomic neuropathy. Effectiveness beyond 2 weeks of treatment has not been established. The continued effectiveness of NORTHERA should be assessed periodically.

2 DOSAGE AND ADMINISTRATION

2.1 Dosing Information

The recommended starting dose of NORTHERA is 100 mg, taken orally three times daily: upon arising in the morning, at midday, and in the late afternoon at least 3 hours prior to bedtime (to reduce the potential for supine hypertension during sleep). Administer NORTHERA consistently, either with food or without food. Take NORTHERA capsule whole. Titrate to symptomatic response, in increments of 100 mg three times daily every 24 to 48 hours up to a maximum dose of 600 mg three times daily (i.e., a maximum total daily dose of 1,800 mg).

Monitor supine blood pressure prior to initiating NORTHERA and after increasing the dose.

Patients who miss a dose of NORTHERA should take their next scheduled dose.

3 DOSAGE FORMS AND STRENGTHS

NORTHERA capsules are available in 100 mg, 200 mg, and 300 mg strengths as specified below.

- 100 mg: Hard gelatin capsules with “Northera” on the white body and “100” on the light blue cap
- 200 mg: Hard gelatin capsules with “Northera” on the white body and “200” on the light yellow cap
- 300 mg: Hard gelatin capsules with “Northera” on the white body and “300” on the light green cap

4 CONTRAINDICATIONS

NORTHERA is contraindicated in patients who have a history of hypersensitivity to the drug or its ingredients [see Warnings and Precautions (5.4)].

5 WARNINGS AND PRECAUTIONS

5.1 Supine Hypertension

NORTHERA therapy may cause or exacerbate supine hypertension in patients with nOH. Patients should be advised to elevate the head of the bed when resting or sleeping. Monitor blood pressure, both in the supine position and in the recommended head-elevated sleeping position. Reduce or discontinue NORTHERA if supine hypertension persists. If supine hypertension is not well-managed, NORTHERA may increase the risk of cardiovascular events, particularly stroke.

5.2 Hyperpyrexia and Confusion

Postmarketing cases of a symptom complex resembling neuroleptic malignant syndrome (NMS) have been reported with NORTHERA use during postmarketing surveillance. Observe patients carefully when the dosage of NORTHERA is changed or when concomitant levodopa is reduced abruptly or discontinued, especially if the patient is receiving neuroleptics.

NMS is an uncommon but life-threatening syndrome characterized by fever or hyperthermia, muscle rigidity, involuntary movements, altered consciousness, and mental status changes. The early diagnosis of this condition is important for the appropriate management of these patients.

5.3 Ischemic Heart Disease, Arrhythmias, and Congestive Heart Failure

NORTHERA may exacerbate existing ischemic heart disease, arrhythmias, and congestive heart failure. Careful consideration should be given to this potential risk prior to initiating therapy in patients with these conditions.

5.4 Allergic Reactions

Hypersensitivity reactions including anaphylaxis, angioedema, bronchospasm, urticaria and rash have been reported in postmarketing experience. Some of these reactions resulted in emergency treatment. If a hypersensitivity reaction occurs, discontinue the drug and initiate appropriate therapy.

This product contains FD&C Yellow No. 5 (tartrazine) which may also cause allergic-type reactions (including bronchial asthma) in certain susceptible persons. Although the overall incidence of FD&C Yellow No. 5 (tartrazine) sensitivity in the general population is low, it is frequently seen in patients who also have aspirin hypersensitivity [see Contraindications (4)].

6 ADVERSE REACTIONS

The following adverse reactions with NORTHERA are included in more detail in the Warnings and Precautions section of the label:

- Supine Hypertension [see Warnings and Precautions (5.1)]
- Hyperpyrexia and Confusion [see Warnings and Precautions (5.2)]
- May exacerbate existing ischemic heart disease, arrhythmias, and congestive heart failure [see Warnings and Precautions (5.3)]

6.1 Clinical Trials Experience

Because clinical trials are conducted under widely varying conditions, adverse reaction rates observed in the clinical trials of a drug cannot be directly compared to rates in the clinical trials of another drug and may not reflect the rates observed in clinical practice.

The safety evaluation of NORTHERA is based on two placebo-controlled studies 1 to 2 weeks in duration (Studies 301 and 302), one 8-week placebo-controlled study (Study 306), and two long-term, open-label extension studies (Studies 303 and 304). In the placebo-controlled studies, a total of 485 patients with Parkinson's disease, multiple system atrophy, pure autonomic failure, dopamine beta-hydroxylase deficiency, or non-diabetic autonomic neuropathy were randomized and treated, 245 with NORTHERA and 240 with placebo [see Clinical Studies (14)].

Placebo-Controlled Experience

The most commonly observed adverse reactions (those occurring at an incidence of greater than 5% in the NORTHERA group and with at least a 3% greater incidence in the NORTHERA group than in the placebo group) in NORTHERA-treated patients during the three placebo-controlled trials were headache, dizziness, nausea, and hypertension. The most common adverse reactions leading to discontinuation from NORTHERA were hypertension or increased blood pressure and nausea.

Table 1. Most Common Adverse Reactions Occurring More Frequently in the NORTHERA Group
 | Study 301 and Study 302 (1 to 2 Weeks Randomized Treatment) |  | Study 306 (8 to 10 Weeks Randomized Treatment)
 | Placebo (N=132) n (%) | NORTHERA (N=131) n (%) | Placebo (N=108) n (%) | NORTHERA (N=114)
 | Placebo (N=132) n (%) | NORTHERA (N=131) n (%) | Placebo (N=108) n (%) | n (%)
Headache | 4 (3.0) | 8 (6.1) | 8 (7.4) | 15 (13.2)
Dizziness | 2 (1.5) | 5 (3.8) | 5 (4.6) | 11 (9.6)
Nausea | 2 (1.5) | 2 (1.5) | 5 (4.6) | 10 (8.8)
Hypertension | 0 | 2 (1.5) | 1 (0.9) | 8 (7.0)

Note: n=number of patients. Adverse reactions that were reported in greater than 5% of patients in the NORTHERA group and with at least a 3% greater incidence in the NORTHERA group than in the placebo group were from Study 306.

Long-Term, Open-Label Trials with NORTHERA
In the long-term, open-label extension studies, a total of 422 patients, mean age 65 years, were treated with NORTHERA for a mean total exposure of approximately one year. The commonly reported adverse events were falls (24%), urinary tract infections (15%), headache (13%), syncope (13%), and dizziness (10%).

6.2 Postmarketing Experience

The following adverse reactions have been identified during post-approval use of NORTHERA. Because these reactions are reported voluntarily from a population of uncertain size, it is not always possible to reliably estimate their frequency or establish a causal relationship to drug exposure.

Cardiac Disorders: Chest pain
Eye Disorders: Blurred vision
Gastrointestinal Disorders: Pancreatitis, abdominal pain, vomiting, diarrhea
General Disorders and Administration Site Conditions: Fatigue
Nervous System Disorders: Cerebrovascular accident
Psychiatric Disorders: Psychosis,hallucination, delirium, agitation, memory disorder

7 DRUG INTERACTIONS

7.1 Drugs that Increase Blood Pressure

Administering NORTHERA in combination with other agents that increase blood pressure (e.g., norepinephrine, ephedrine, midodrine, and triptans) would be expected to increase the risk for supine hypertension.

7.2 Parkinson's Medications

Dopa-decarboxylase inhibitors may require dose adjustments for NORTHERA.

7.3 Non-selective MAO Inhibitors

The concomitant use of selective MAO-B inhibitors, such as rasagiline or selegiline, was permitted in the NORTHERA clinical trials. However, based on mechanism of action, the use of non-selective MAO inhibitors and linezolid should be avoided as there is a potential for increased blood pressure when taken with NORTHERA.

8 USE IN SPECIFIC POPULATIONS

8.1 Pregnancy

Risk Summary

There are no available data on use of NORTHERA in pregnant women and risk of major birth defects or miscarriage. NORTHERA did not produce significant reproductive toxicity in pregnant female rats or rabbits or in their fetuses. However, when pregnant female rats were dosed during days 7-17 of gestation (the period of fetal organogenesis) with doses of NORTHERA corresponding to 0.3, 1 and 3 times the maximum recommended daily dose of 1,800 mg in a 60 kg patient, based on body surface area, and when their male and female offspring (who were exposed only during fetal life) were subsequently bred, the female offspring exhibited a dose-dependent reduction in the number of live fetuses across all three doses and an increased number of embryonic/fetal deaths at the two higher doses (see Data).

The estimated background risk of major birth defects and miscarriage in the indicated population is unknown. In the U.S. general population, the estimated background risk of major birth defects and miscarriage in clinically recognized pregnancies is 2 to 4% and 15 to 20%, respectively.

Data

Animal Data

During a multigenerational reproductive toxicity study in rats, pregnant females were dosed during days 7-17 of gestation (the period of fetal organogenesis) with doses of NORTHERA corresponding to 0.3, 1 and 3 times the maximum recommended daily dose of 1,800 mg in a 60 kg patient. Reduced weight gain, renal lesions, and a small number of deaths were observed in females treated with the two higher doses. When their male and female offspring (who were exposed to NORTHERA only during fetal life) were subsequently bred, the female offspring exhibited a dose-dependent reduction in the number of live fetuses across all three doses and an increased number of embryonic/fetal deaths at the two higher doses.

8.2 Lactation

Risk Summary

There is no information regarding the presence of NORTHERA or its active metabolite(s) in human milk, the effects of NORTHERA on the breastfed child, nor the effects of NORTHERA on milk production/excretion. Droxidopa is present in rat milk with peak concentrations seen 4 hours after oral drug administration and drug excretion into milk still occurring 48 hours after administration (see Data). However, due to species-specific differences in lactation physiology, animal lactation data typically do not reliably predict levels in humans. Because of the potential for serious adverse reactions, including reduced weight gain in breastfed infants, advise a woman not to breastfeed during treatment with NORTHERA.

Data

Animal Data

In rats, oral administration of droxidopa resulted in excretion into breast milk with peak concentrations seen 4 hours after administration, and excretion still occurring 48 hours after administration. When the drug was administered to nursing dams during the period of lactation at a dose corresponding to 3 times the maximum recommended daily dose of 1,800 mg in a 60 kg patient when based on body surface area, reduced weight gain and reduced survival were observed in the offspring. Despite the observed decreased weight gain, physical development was normal (with respect to timing and organ morphology).

8.4 Pediatric Use

The safety and effectiveness of NORTHERA in pediatric patients have not been established.

8.5 Geriatric Use

A total of 197 patients with symptomatic nOH aged 75 years or above were included in the NORTHERA clinical program. No overall differences in safety or effectiveness were observed between these patients and younger patients, and other reported clinical experience has not identified differences in responses between the elderly and younger patients, but greater sensitivity of some older individuals cannot be ruled out.

8.6 Renal Impairment

NORTHERA and its metabolites are primarily cleared renally. Patients with mild or moderate renal impairment (GFR greater than 30 mL/min) were included in clinical trials and did not have a higher frequency of adverse reactions. Clinical experience with NORTHERA in patients with severe renal function impairment (GFR less than 30 mL/min) is limited.

10 OVERDOSAGE

10.1 Symptoms

There have been cases of overdose reported during postmarketing surveillance. A patient ingested 7,700 mg of droxidopa and experienced a hypertensive crisis that resolved promptly with treatment. Another patient treated with a total daily dose of 2,700 mg of NORTHERA experienced hypertension and an intracranial hemorrhage.

10.2 Treatment

There is no known antidote for NORTHERA overdosage. In case of an overdose that may result in an excessively high blood pressure, discontinue NORTHERA and treat with appropriate symptomatic and supportive therapy. Counsel patients to remain in a standing or seated position until their blood pressure drops below an acceptable limit.

11 DESCRIPTION

NORTHERA capsules contain droxidopa, which is a synthetic amino acid precursor of norepinephrine, for oral administration. Chemically, droxidopa is (–)-threo-3-(3,4-Dihydroxyphenyl)-L-serine. It has the following structural formula:

Droxidopa is an odorless, tasteless, white to off-white crystals or crystalline powder. It is slightly soluble in water, and practically insoluble in methanol, glacial acetic acid, ethanol, acetone, ether, and chloroform. It is soluble in dilute hydrochloric acid. It has a molecular weight of 213.19 and a molecular formula of C9H11NO5.

NORTHERA capsules also contain the following inactive ingredients: mannitol, corn starch, and magnesium stearate. The capsule shell is printed with black ink. The black inks contain shellac glaze, ethanol, iron oxide black, isopropyl alcohol, n-butyl alcohol, propylene glycol, and ammonium hydroxide. The capsule shell contains the following inactive ingredients: 100 mg – gelatin, titanium dioxide, FD&C Blue No. 2, black and red iron oxide; 200 mg – gelatin, titanium dioxide, FD&C Blue No. 2, black and yellow iron oxide; 300 mg – gelatin, titanium dioxide, FD&C Blue No. 1, FD&C Yellow No. 5 (tartrazine), and FD&C Red No. 40. NORTHERA capsules differ in size and color by strength [see Dosage Forms and Strengths (3)].

12 CLINICAL PHARMACOLOGY

12.1 Mechanism of Action

The exact mechanism of action of NORTHERA in the treatment of neurogenic orthostatic hypotension is unknown. NORTHERA is a synthetic amino acid analog that is directly metabolized to norepinephrine by dopa-decarboxylase, which is extensively distributed throughout the body. NORTHERA is believed to exert its pharmacological effects through norepinephrine and not through the parent molecule or other metabolites. Norepinephrine increases blood pressure by inducing peripheral arterial and venous vasoconstriction. NORTHERA in humans induces small and transient rises in plasma norepinephrine.

12.2 Pharmacodynamics

Peak droxidopa plasma concentrations are associated with increases in systolic and diastolic blood pressures. Droxidopa has no clinically significant effect on standing or supine heart rates in patients with autonomic failure.

Cardiac Electrophysiology
No prolongation of the QTc interval was observed with NORTHERA at single oral doses up to 2,000 mg, as shown in a dedicated thorough QT study.

12.3 Pharmacokinetics

Absorption
Peak plasma concentrations (Cmax) of droxidopa were reached by 1 to 4 hours post-dose (mean of approximately 2 hours) in healthy volunteers. High-fat meals have a moderate impact on droxidopa exposure with Cmax and area under the plasma concentration-time curve (AUC) decreasing by 35% and 20%, respectively. The Cmax was delayed by approximately 2 hours with a high-fat meal.

Distribution
Pre-clinical studies suggest that droxidopa can cross the blood brain barrier. Droxidopa exhibits plasma protein binding of 75% at 100 ng/mL and 26% at 10,000 ng/mL. The estimated apparent volume of distribution of droxidopa is about 200 L in humans.

Elimination

The total clearance of droxidopa after oral administration (CL/F) was approximately 400 mL/hr following administration of a single 300 mg dose.

Metabolism

The metabolism of droxidopa is mediated by catecholamine pathway and not through the cytochrome P450 system. Droxidopa is initially converted to methoxylated dihydroxyphenylserine (3-OM-DOPS), a major metabolite, by catechol-O-methyltransferase (COMT), to norepinephrine by DOPA decarboxylase (DDC), or to protocatechualdehyde by DOPS aldolase. After oral dosing in humans, plasma norepinephrine levels peak within 3 to 4 hours but are generally very low (less than 1 ng/mL) and variable with no consistent relationship with dose. The contribution of the metabolites of droxidopa other than norepinephrine to its pharmacological effects is not well understood.

Excretion

The mean elimination half-life of droxidopa is approximately 2.5 hours in humans. The major route of elimination of droxidopa and its metabolites is via the kidneys in both animals and in humans. Studies in animals with radiolabeled drug showed that ~75% of the administered radioactivity was excreted in urine within 24 hours of oral dosing.

Specific Populations

There are no clinically relevant effects of age, body mass index, or sex on the pharmacokinetics of droxidopa. A population pharmacokinetic analysis suggests that hepatic function, assessed by aspartate aminotransferase (AST), alanine aminotransferase (ALT), alkaline phosphatase, and total bilirubin, did not influence the exposure to droxidopa. The controlled clinical trials included patients with mild to moderate renal impairment. No dose adjustments are required in patients with mild to moderate renal impairment.

Drug Interaction Studies

No dedicated drug-drug interaction studies were performed for droxidopa. Patients in the Phase 3 trials with NORTHERA received concomitant levodopa/carbidopa, dopamine agonists, MAO-B inhibitors, COMT inhibitors and other medications used to treat Parkinson’s disease. Carbidopa, a peripheral dopa-decarboxylase inhibitor, could prevent the conversion of NORTHERA to norepinephrine outside of the central nervous system (CNS). Patients taking NORTHERA with L-DOPA/dopa-decarboxylase inhibitor combination drugs had decreased clearance of NORTHERA, an increase in overall exposure (AUC) to droxidopa of approximately 100%, and an increase in overall exposure to 3-OM-DOPS of approximately 50%. However, in clinical trials, it was found that the decreased clearance was not associated with a significant need for a different treatment dose or increases in associated adverse events. Dopamine agonists, amantadine derivatives, and MAO-B inhibitors do not appear to affect NORTHERA clearance, and no dose adjustments are required.

13 NONCLINICAL TOXICOLOGY

13.1 Carcinogenesis, Mutagenesis, Impairment of Fertility

Long-term studies have been conducted at dosages up to 1,000 mg/kg/day in mice and up to 100 mg/kg/day in rats with no indication of carcinogenic effects. Based on dose per unit body surface area, these two doses correspond to approximately 3 and 0.5 times, respectively, the maximum recommended total daily dose of 1,800 mg in a 60 kg patient. Droxidopa was clastogenic in Chinese hamster ovary cells (chromosome aberration assay), but was not mutagenic in bacteria (Ames assay), and was not clastogenic in a mouse micronucleus assay.

Studies in rats show that droxidopa has no effect on fertility.

13.2 Animal Toxicology and/or Pharmacology

In long-term chronic toxicity studies, rats and mice treated for 52 and 80 weeks, respectively, at doses up to 300 mg/kg/day in rats and 1,000 mg/kg/day in mice had increased incidences of renal and cardiac lesions (rats and mice) and deaths (rats only). The doses at which these effects were not seen represented 0.2 and 0.3 times, in rats and mice, respectively, the maximum recommended total daily dose of 1,800 mg in a 60 kg patient, when based on body surface area.

No signs of toxicity were observed in monkeys or dogs given droxidopa for 13 weeks at doses 32 times (3,000 mg/kg/day) and 37 times (2,000 mg/kg/day), respectively, the maximum human dose.

14 CLINICAL STUDIES

14.1 Studies in Neurogenic Orthostatic Hypotension

Clinical studies (described below) examined the efficacy of NORTHERA in the short-term (1 to 2 weeks) and over longer-term periods (8 weeks; 3 months). Studies 301 and 306B showed a treatment effect of NORTHERA at Week 1, but none of the studies demonstrated continued efficacy beyond 2 weeks of treatment.

Study 306B was a multi-center, double-blind, randomized, placebo-controlled, parallel-group study in patients with symptomatic nOH and Parkinson’s disease. Patients entering the study were required to have a decrease of at least 20 mm Hg or 10 mm Hg, respectively, in systolic or diastolic blood pressure, within 3 minutes after standing, as well as symptoms associated with neurogenic orthostatic hypotension. The study had an initial dose titration period that lasted up to 2 weeks in which patients received placebo or 100 to 600 mg of NORTHERA three times daily, followed by an 8-week treatment period.

Efficacy was measured using the OHSA Item #1 score (“dizziness, lightheadedness, feeling faint, and feeling like you might black out”) at Week 1, in patients who had completed titration and 1 week of maintenance therapy.

A total of 171 patients were enrolled, and 147 patients were included in the efficacy analysis. The mean age was 72 years, and patients were mostly Caucasian. During the study, 94% of placebo-treated patients and 88% on NORTHERA were taking dopa-decarboxylase inhibitors; 17% of placebo-treated patients and 26% on NORTHERA were taking fludrocortisone. There were more premature discontinuations in the NORTHERA group (28%) than in the placebo group (20%).

In both groups, the mean baseline dizziness score was 5.1 on an 11-point scale. At Week 1, patients showed a statistically significant mean 0.9 unit decrease in dizziness with NORTHERA versus placebo (P=0.028), but the effect did not persist beyond Week 1. The data at all time points are shown in Figure 1.

Patients receiving NORTHERA also had a greater increase, compared to placebo, in the Week 1 lowest standing systolic blood pressure within 3 minutes after standing (5.6 mm Hg; P=0.032).

Figure 1. Mean Change in OHSA Item 1 Score by Week in Study 306B

Note: The graph is based on observed data only. The error bars are the 95% confidence interval of the mean change from baseline in OHSA Item 1 scores.

Figure 2. Distribution of Patients by Change in OHSA Item 1, Baseline to Week 1, in Study 306B

Figure 2 shows the distribution of changes from Baseline to Week 1 in the OHSA Item #1 score. Overall the figure shows that patients treated with NORTHERA improved more than those treated with placebo.

Study 301 was a multicenter, multinational, double-blind, randomized, placebo-controlled, parallel-group study in patients with symptomatic neurogenic orthostatic hypotension. The study included an initial open-label dose titration period, a 7-day washout period, and a randomized double-blind 7-day treatment period. To be eligible for enrollment, patients were required to have a decrease in systolic or diastolic blood pressure of at least 20 or 10 mm Hg, respectively, within 3 minutes after standing. The study was enriched, such that only patients who had been identified as "responders" during the titration period were randomized to NORTHERA or placebo. To be considered a responder, a patient had to demonstrate improvement on the OHSA Item #1 score by at least 1 point, as well as an increase in systolic blood pressure of at least 10 mm Hg post-standing, during the open-label dose titration period. Patients who dropped out during the titration period because of side effects or other reasons were also not included in the double-blind portion of the study.

Patients had a primary diagnosis of Parkinson’s disease (n=60), pure autonomic failure (n=36), or multiple system atrophy (n=26). The mean age was 60 years, and most were Caucasian. 45% of patients were taking dopa-decarboxylase inhibitors, and 29% were taking fludrocortisone.

Efficacy was measured using the Orthostatic Hypotension Questionnaire (OHQ), a patient-reported outcome that measures symptoms of nOH and their impact on the patient’s ability to perform daily activities that require standing and walking. The OHQ includes OHSA Item #1 as one of several components. A statistically significant treatment effect was not demonstrated on OHQ (treatment effect of 0.4 unit, P=0.19).

The mean baseline dizziness score on OHSA Item #1 (“dizziness, lightheadedness, feeling faint, and feeling like you might black out”) was 5.2 units on an 11-point scale. At Week 1 of treatment, patients showed a mean 0.7 unit decrease in dizziness with NORTHERA versus placebo (P=0.06).

Study 302 (n=101) was a placebo-controlled, 2-week randomized withdrawal study of NORTHERA in patients with symptomatic nOH. Study 303 (n=75) was an extension of Studies 301 and 302, where patients received their titrated dose of NORTHERA for 3 months and then entered a 2-week randomized withdrawal phase. Neither study showed a statistically significant difference between treatment arms on its primary endpoint. Considering these data, the effectiveness of NORTHERA beyond 2 weeks is uncertain, and patients should be evaluated periodically to determine whether NORTHERA is continuing to provide a benefit.

16 HOW SUPPLIED/STORAGE AND HANDLING

16.1 How Supplied

NORTHERA capsules are supplied in the following dosage strengths:

100 mg: Hard gelatin, size 3 capsule, with an opaque light blue cap and an opaque white body, printed with “Northera” on body and “100” on cap, filled with a white to light brown powder.

200 mg: Hard gelatin, size 2 capsule, with an opaque light yellow cap and an opaque white body, printed with “Northera” on body and “200” on cap, filled with a white to light brown powder.

300 mg: Hard gelatin, size 1 capsule, with an opaque light green cap and an opaque white body, printed with “Northera” on body and “300” on cap, filled with a white to light brown powder.

100 mg 90-count bottle (NDC code# 67386-820-19)

200 mg 90-count bottle (NDC code# 67386-821-19)

300 mg 90-count bottle (NDC code# 67386-822-19)

16.2 Storage and Handling

NORTHERA capsules should be stored at 20°C to 25°C (68°F to 77°F); excursions permitted to 15°C to 30°C (59°F to 86°F) [see USP Controlled Room Temperature].

17 PATIENT COUNSELING INFORMATION

Elevations in Blood Pressure
Counsel patients that NORTHERA causes elevations in blood pressure and increases the risk of supine hypertension, which could lead to strokes, heart attacks, and death. Instruct patients to rest and sleep in an upper-body elevated position and monitor blood pressure. Instruct patients how to manage observed blood pressure elevations. To reduce the risk of supine hypertension, in addition to raising the upper body, the late afternoon dose of NORTHERA should be taken at least three hours before bedtime [see Warnings and Precautions (5.1)].

Concomitant Treatments
Counsel patients about the concomitant use of drugs to treat other conditions that may have an additive effect with NORTHERA [see Drug Interactions (7)].

Allergic Reactions
Counsel patients to discontinue NORTHERA and seek immediate medical attention if any signs or symptoms of a hypersensitivity reaction such as anaphylaxis, angioedema, bronchospasm, urticaria or rash occur [see Warnings and Precautions (5.4)].

Lactation

Advise women not to breastfeed during treatment with NORTHERA [see Use in Specific Populations (8.2)].

Food
Patients should take NORTHERA the same way each time, either with food or without food [see Dosage and Administration (2.1)].

Missed Dose
If a dose is missed, patients should take the next dose at the regularly scheduled time and should not double the dose.

Manufactured by:
Patheon, Whitby, ON L1N 5Z5, Canada

For:
Lundbeck, Deerfield, IL 60015, U.S.A.

NORTHERA is a registered trademark of Lundbeck NA Ltd.

PRINCIPAL DISPLAY PANEL

NDC 67386-820-19
90 Capsules
Northera™
(droxidopa) capsules
100 mg
Rx Only

PRINCIPAL DISPLAY PANEL

NDC 67386-821-19
90 Capsules
Northera™
(droxidopa) capsules
200 mg
Rx Only

PRINCIPAL DISPLAY PANEL

NDC 67386-822-19
90 Capsules
Northera™
(droxidopa) capsules
300 mg
Rx Only

PRINCIPAL DISPLAY PANEL

NDC 67386-820-99
90 Capsules
Northera™
(droxidopa) capsules
100 mg
Rx Only

Professional Sample